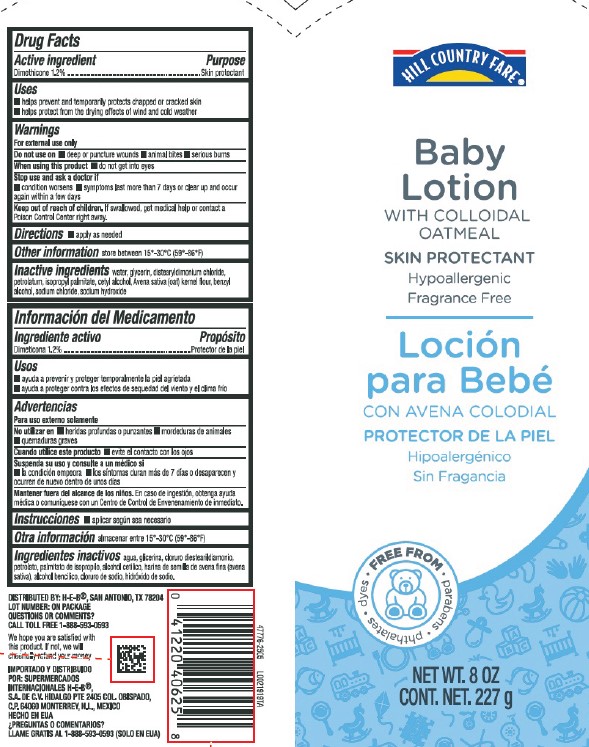 DRUG LABEL: Dimethicone
NDC: 37808-496 | Form: LOTION
Manufacturer: H E B
Category: otc | Type: HUMAN OTC DRUG LABEL
Date: 20260224

ACTIVE INGREDIENTS: DIMETHICONE 12 mg/1 g
INACTIVE INGREDIENTS: WATER; GLYCERIN; DISTEARYLDIMONIUM CHLORIDE; PETROLATUM; ISOPROPYL PALMITATE; CETYL ALCOHOL; OATMEAL; BENZYL ALCOHOL; SODIUM CHLORIDE; SODIUM HYDROXIDE

HEB_HCF 496.000/496AA
Daily Baby Lotion with Colloidal Oatmeal

Active ingredient

Dimethicone 1.2%

Purpose

Skin protectant

Uses

- helps prevent and temporarily protects chapped or cracked skin
- helps protect from the drying effects of wind and cold weather

Warnings

For external use only

Do not use on

- deep or puncture wounds
- animal bites
- serious burns

When using this product

do not get into eyes

Stop use and ask a doctor if

- condition worsens
- symptoms last more then 7 days or clear up and occur again within a few days

Keep out of reach of children.

If swallowed, get medical help or contact Poison Control right away.

Directions

- apply as needed

Other information

store between 15°-30°C (59°-86°F)

inactive ingredients

water, glycerin, distearyldimonium chloride, petrolatum, isopropyl palmitate, cetyl alcohol, Avena sativa (oat) kernel flour, benzyl alcohol, sodium chloride, sodium hydroxide

ADVERSE REACTION

DISTRIBUTED BY: H-E-B®, SAN ANTONIO, TN 78204

LOT NUMBER: ON PACKAGE

QUESTIONS OR COMMENTS?

CALL TOLL FREE 1-888-593-0593

We hope you are satisfied with this product.

If not, we will cheerfully refund your money.

Principal panel display

HILL COUNTRY FARE®

Baby Lotion

WITH COLLOIDAL OATMEAL

SKIN PROTECTANT

Hypoallergenic

Fragrance Free

Free From

- Parabens
- Phthalates
- Dyes

NET WT 8 OZ

CONT. NET. 227 g